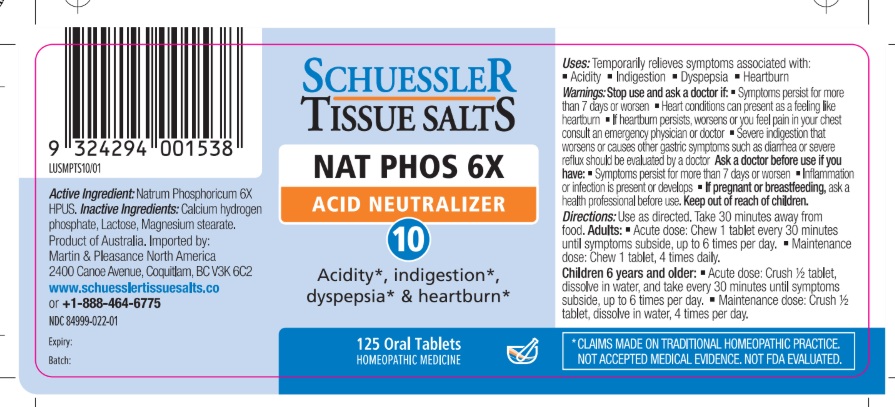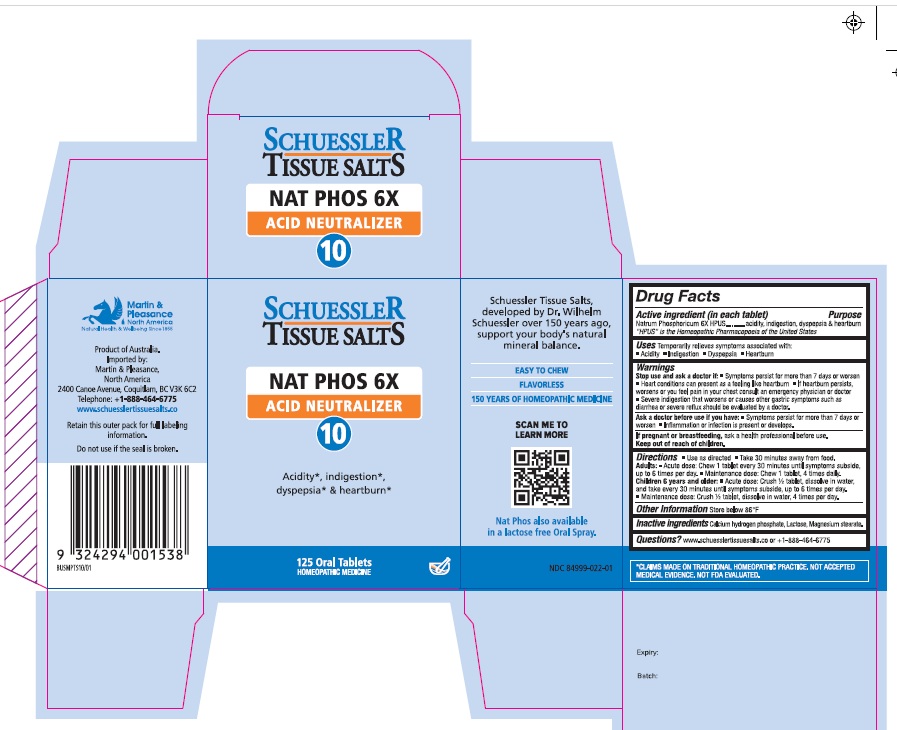 DRUG LABEL: Schuessler Tissue Salts Nat Phos Acid Neutralizer 10
NDC: 84999-022 | Form: TABLET, CHEWABLE
Manufacturer: Martin & Pleasance Pty Ltd
Category: homeopathic | Type: HUMAN OTC DRUG LABEL
Date: 20250804

ACTIVE INGREDIENTS: SODIUM PHOSPHATE, DIBASIC, ANHYDROUS 6 [hp_X]/1 1
INACTIVE INGREDIENTS: LACTOSE MONOHYDRATE; MAGNESIUM STEARATE; ANHYDROUS DIBASIC CALCIUM PHOSPHATE

Active Ingredients Purpose

Natrum Phosphoricum 6X HPUS acidity, indigestion, dyspepsia & heartburn

" HPUS" is the Homeopathic Pharmacopoeia of the United States

Uses

Temporarily relieves symptoms associated with

- Acidity
- Indigestion
- Dyspepsia
- Heartburn

Warnings

Stop use and ask a doctor if:

- Symptoms persist for more than 7 days or worsen
- Heart conditions can present as a feeling like heartburn
- If heartburn persists, worsens, or you feel pain in your chest, consult an emergency physician or doctor
- Severe indigestion that worsens or causes other gastric symptoms such as diarrhea or severe reflux should be evaluated by a doctor

Ask a doctor before use if you have:

- Fever that gets worse or lasts more than 3 days
- Symptoms that persist for more than 7 days or worsen
- Inflammation or infection that is present or develops

If pregnant or breastfeeding:Ask a health professional before use.

Keep out of reach of children.

Directions

- Use as directed
- Take 30 minutes away from food

Adults: Acute dose: Chew 1 tablet every 30 minutes until symptoms subside up to 6 times per day.

Maintenance dose: Chew 1 tablet, 4 times daily.

Children 6 years and older: Acute dose: Crush 1/2 tablet, dissolve in water, and take every 30 minutes until symptoms subside, up to six times per day.

Maintenance dose :Crush 1/2 tablet, dissolve in water, 4 times per day.

Other Information

Store below 86°F

Inactive Ingredients

Calcium hydrogen phosphate, Lactose, Magnesium stearate

Questions?www.schuesslertissuesalts.co or + 1-888-464-6775